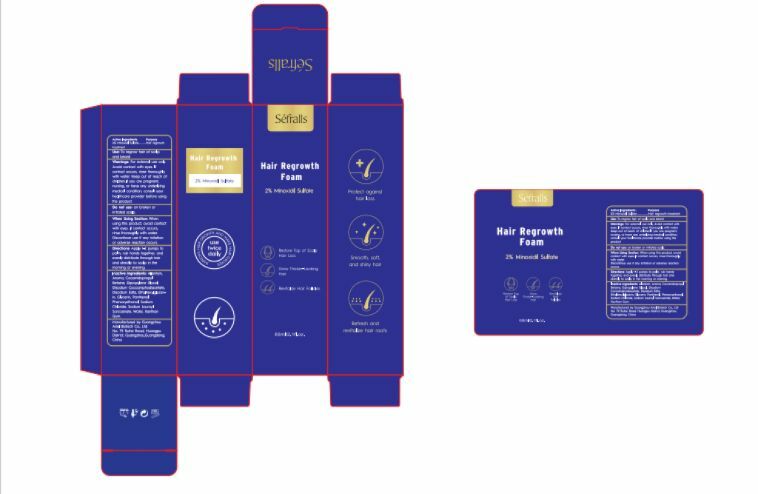 DRUG LABEL: Hair Regrowth Foam
NDC: 84148-006 | Form: AEROSOL, FOAM
Manufacturer: Guangzhou Ariel Biotech Co., Ltd.
Category: otc | Type: HUMAN OTC DRUG LABEL
Date: 20240718

ACTIVE INGREDIENTS: MINOXIDIL SULFATE 2 g/100 mL
INACTIVE INGREDIENTS: PHENOXYETHANOL; WATER; SODIUM CHLORIDE; XANTHAN GUM; SODIUM LAUROYL SARCOSINATE; PANTHENOL; GLYCERIN; ALLANTOIN; AROMADENDRIN; COCAMIDOPROPYL BETAINE; DIPROPYLENE GLYCOL; DISODIUM COCOAMPHODIACETATE; EDETATE DISODIUM; ETHYLHEXYLGLYCERIN

84148-006

Active Ingredient(s)

Minoxidil Sulfate 2%

Purpose

Hair regrowth treatment

Use

Use: To regrow hair of scalp and beard

Warnings

Warnings: For external use only. Avoid contact with eyes. If contact occurs, rinse thoroughly with water. Keep out of reach of
children.lf you are pregnant, nursing, or have any underlying medical condition, consult your healthcare provider before using
the product.

Do not use: on broken or irritated scalp.

WHEN USING

When Using Section: When using this product, avoid contact with eyes. If contact occurs,
rinse thoroughly with water. Discontinve use if any irritation or adverse reaction occurs.

STOP USE

●Chest pain, rapid heartbeat, faintness or dizziness occurs.
●Scalp iritation or redness occurs.

Keep out of reach of children.

Directions

Directions: Apply 1-2 pumps to palm, rub hands together, and evenly distribute through hair and
directly to scalp in the morning or evening.

Other information

No Data

Inactive ingredients

Inactive ingredients: Allantoin, Aroma, Cocamidopropyl Betaine, Dipropylene Glycol Disodium Cocoamphodiacetate, Disodium Edta,
Ethylhexylglycerin, Glycerin, Panthenol, Phenoxyethano, Sodium Chloride, Sodium Lauroyl Sarcosinate, Water, Xanthan Gum.